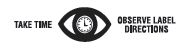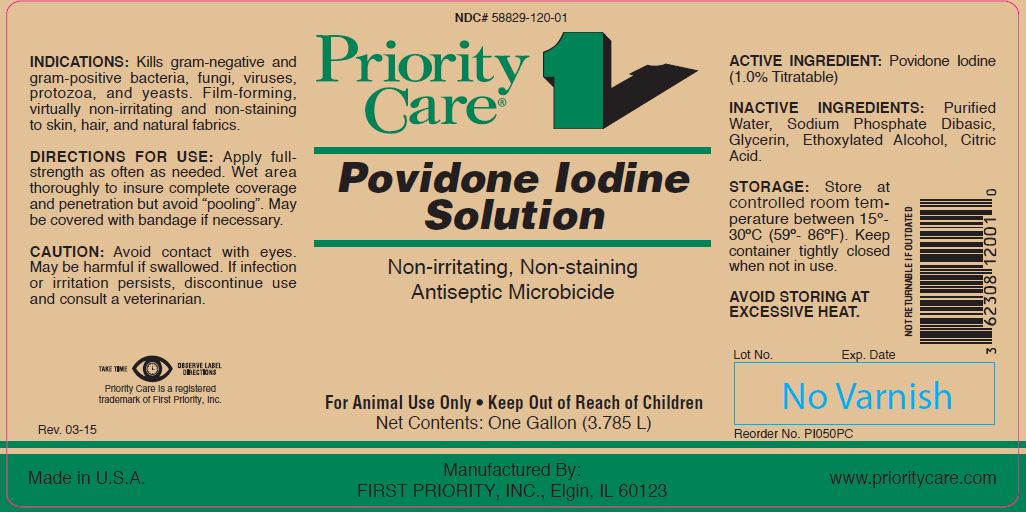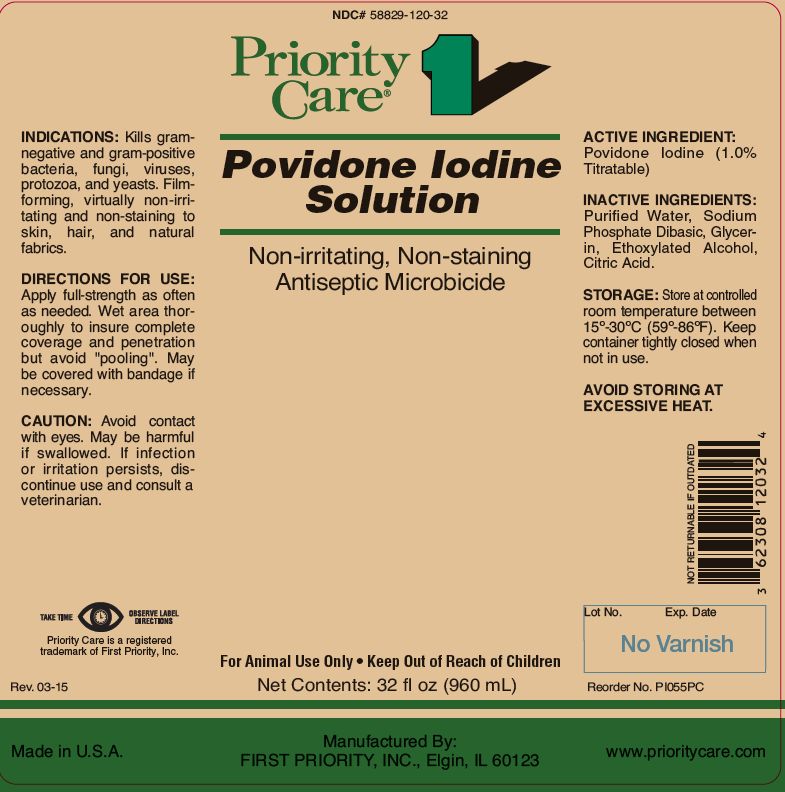 DRUG LABEL: POVIDONE IODINE
NDC: 58829-120 | Form: SOLUTION
Manufacturer: FIRST PRIORITY INCORPORATED
Category: animal | Type: OTC ANIMAL DRUG LABEL
Date: 20181106

ACTIVE INGREDIENTS: POVIDONE-IODINE 65.9 g/1 L

Povidone Iodine Solution

PURPOSE

Non-irritating, Non-staining Antiseptic Microbicide

KEEP OUT OF REACH OF CHILDREN

For Animal Use Only • Keep Out of Reach of Children

INDICATIONS:

Kills gram-negative and gram-positive bacteria, fungi, viruses, protozoa, and yeasts. Film-forming, virtually non-irritating and non-staining to skin, hair, and natural fabrics.

DIRECTIONS FOR USE:

Apply full-strength as often as needed. Wet area thoroughly to insure complete coverage and penetration but avoid “pooling”. May be covered with bandage if necessary.

CAUTION:

Avoid contact with eyes. May be harmful if swallowed. If infection or irritation persists, discontinue use and consult a veterinarian.

ACTIVE INGREDIENT:

Povidone Iodine (1.0% Titratable)

INACTIVE INGREDIENTS:

Purified Water, Sodium Phosphate Dibasic, Glycerin, Ethoxylated Alcohol, Citric Acid.

STORAGE:

Store at controlled room temperature between 15º-30ºC (59º-86ºF). Keep container tightly closed when not in use.

AVOID STORING AT EXCESSIVE HEAT.

Net Contents:

32 fl oz (960 mL) Reorder No. PI055PC

One Gallon (3.785 L) Reorder No. PI050PC

INFORMATION FOR OWNERS/CAREGIVERS

Priority Care is a registered trademark of First Priority, Inc.

Made in U.S.A.

Manufactured By: FIRST PRIORITY, INC., Elgin, IL 60123

www.prioritycare.com

NOT RETURNABLE IF OUTDATED